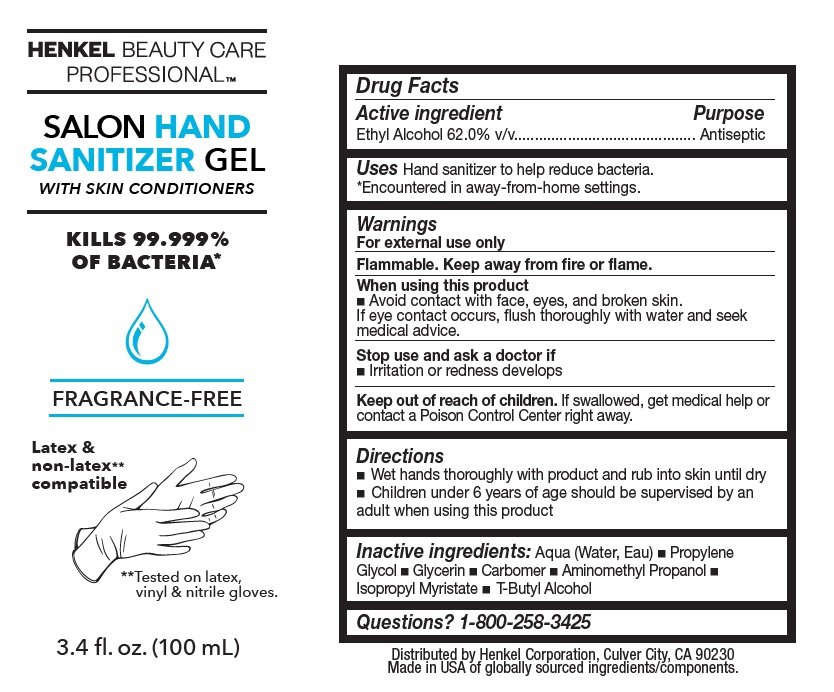 DRUG LABEL: Henkel Beauty Care Professional
NDC: 50663-005 | Form: GEL
Manufacturer: Zotos International Inc
Category: otc | Type: HUMAN OTC DRUG LABEL
Date: 20201102

ACTIVE INGREDIENTS: ALCOHOL 60.15 mL/100 mL
INACTIVE INGREDIENTS: WATER 38.19 mL/100 mL; ISOPROPYL MYRISTATE 0.14 mL/100 mL; TERT-BUTYL ALCOHOL 0.07 mL/100 mL; PROPYLENE GLYCOL 0.5 mL/100 mL; GLYCERIN 0.49 mL/100 mL; CARBOMER HOMOPOLYMER, UNSPECIFIED TYPE 0.29 mL/100 mL; AMINOMETHYLPROPANOL 0.14 mL/100 mL

Henkel Beauty care professional Salon Hand Sanitizer Gel

Active Ingredient(s)

Ethyl Alcohol 62% v/v.

Purpose

Antiseptic

Uses

Hand Sanitizer to help reduce bacteria.

*Encountered in away-from-home settings.

Warnings

For external use only.

Flammable. Keep away from fire or flame

When using this product

avoid contact with face, eyes, and broken skin. if eye contact occurs, flush thoroughly with water and seek medical advice.

Stop use and ask a doctor if

irritation or redness develops.

Keep out of reach of children.

If swallowed, get medical help or contact a Poison Control Center right away.

Directions

Wet hands thoroughly with product and rub into skin until dry.

Children under 6 years of age should be supervised by an adult when using this product.

Inactive ingredients

Aqua (Water, Eau)• Propylene Glycol• Glycerin• Carbomer • Aminomethyl Propanol • lsopropyl Myristate • T-Butyl Alcohol

Questions?

1-800-258-3425

Legal entity

Distributed by Henkel Corporation, Culver City, CA 90230
Made in USA of globally sourced ingredients/components.